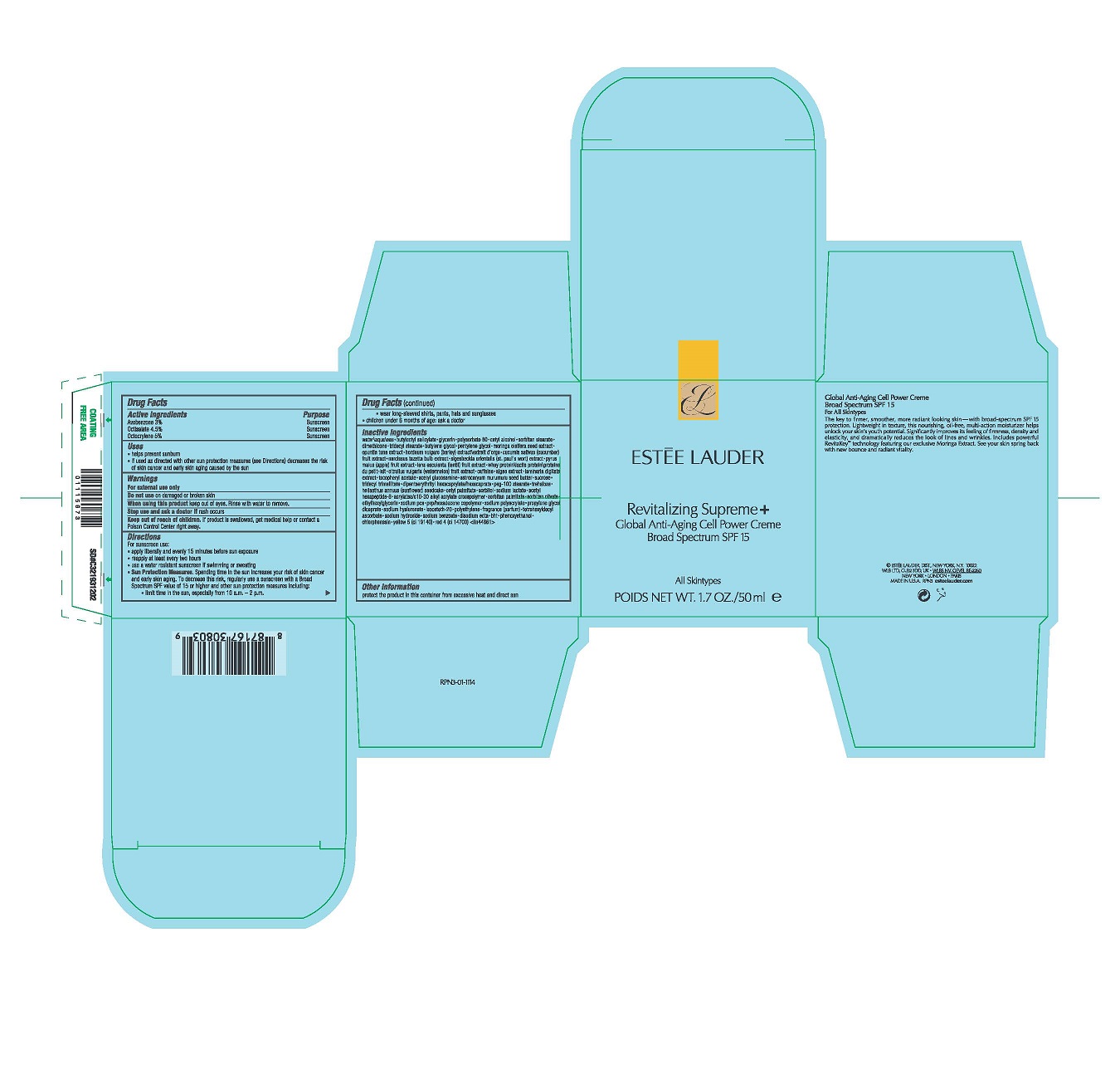 DRUG LABEL: REVITALIZING SUPREME PLUS GLOBAL ANTI-AGING CELL POWER CREME BROAD SPECTRUM SPF 15
NDC: 11559-056 | Form: CREAM
Manufacturer: ESTEE LAUDER INC
Category: otc | Type: HUMAN OTC DRUG LABEL
Date: 20241225

ACTIVE INGREDIENTS: AVOBENZONE 30 mg/1 mL; OCTISALATE 45 mg/1 mL; OCTOCRYLENE 50 mg/1 mL
INACTIVE INGREDIENTS: N-ACETYLGLUCOSAMINE; ASTROCARYUM MURUMURU SEED BUTTER; SUCROSE; TRIDECYL TRIMELLITATE; DIPENTAERYTHRITYL HEXACAPRYLATE/HEXACAPRATE; PEG-100 STEARATE; TREHALOSE; HELIANTHUS ANNUUS SEEDCAKE; CETYL PALMITATE; SORBITOL; SODIUM LACTATE; ACETYL HEXAPEPTIDE-8; CARBOMER INTERPOLYMER TYPE A (ALLYL SUCROSE CROSSLINKED); SORBITAN MONOPALMITATE; SORBITAN OLIVATE; ETHYLHEXYLGLYCERIN; SODIUM PYRROLIDONE CARBOXYLATE; PROPYLENE GLYCOL DICAPRATE; HYALURONATE SODIUM; ISOCETETH-20; HIGH DENSITY POLYETHYLENE; TETRAHEXYLDECYL ASCORBATE; SODIUM HYDROXIDE; SODIUM BENZOATE; EDETATE DISODIUM ANHYDROUS; PHENOXYETHANOL; BUTYLATED HYDROXYTOLUENE; CHLORPHENESIN; FD&C YELLOW NO. 5; FD&C RED NO. 4; WATER; BUTYLOCTYL SALICYLATE; GLYCERIN; POLYSORBATE 60; CETYL ALCOHOL; SORBITAN MONOSTEARATE; DIMETHICONE; TRIDECYL STEARATE; BUTYLENE GLYCOL; PENTYLENE GLYCOL; MORINGA OLEIFERA LEAF; BARLEY; CUCUMBER; NARCISSUS TAZETTA BULB; APPLE; LENS CULINARIS FRUIT; WHEY; WATERMELON; CAFFEINE; LAMINARIA DIGITATA; .ALPHA.-TOCOPHEROL ACETATE

REVITALIZING SUPREME + GLOBAL ANTI-AGING CELL POWER CRÈME BROAD SPECTRUM SPF 15

Drug Facts

ACTIVE INGREDIENT

Active ingredients | Purpose
Avobenzone 3.0% | Sunscreen
Octisalate 4.5% | Sunscreen
Octocrylene 5.0% | Sunscreen

Uses

- helps prevent sunburn
- if used as directed with other sun protection measures (see Directions) decreases the risk of skin cancer and early skin aging caused by the sun

Warnings

For external use only

Do not use on damaged or broken skin

When using this product keep out of eyes. Rinse with water to remove.

Stop use and ask a doctor if rash occurs

Keep out of reach of children. If product is swallowed, get medical help or contact a Poison Control Center right away.

Directions

For sunscreen use:

- apply liberally and evenly 15 minutes before sun exposure
- reapply at least every two hours
- use a water resistant sunscreen if swimming or sweating
- Sun Protection Measures. Spending time in the sun increases your risk of skin cancer and early skin aging. To decrease this risk, regularly use a sunscreen with a Broad Spectrum SPF value of 15 or higher and other sun protection measures including:
  - limit time in the sun, especially from 10 a.m. – 2 p.m.
  - wear long-sleeved shirts, pants, hats and sunglasses
- children under 6 months of age: ask a doctor

Inactive ingredients

water\aqua\eau • butyloctyl salicylate • glycerin • polysorbate 60 • cetyl alcohol • sorbitan stearate • dimethicone • tridecyl stearate • butylene glycol • pentylene glycol • moringa oleifera seed extract • opuntia tuna extract • hordeum vulgare (barley) extract\extrait d'orge • cucumis sativus (cucumber) fruit extract • narcissus tazetta bulb extract • sigesbeckia orientalis (st. paul's wort) extract • pyrus malus (apple) fruit extract • lens esculenta (lentil) fruit extract • whey protein\lactis protein\proteine du petit-lait • citrullus vulgaris (watermelon) fruit extract • caffeine • algae extract • laminaria digitata extract • tocopheryl acetate • acetyl glucosamine • astrocaryum murumuru seed butter • sucrose • tridecyl trimellitate • dipentaerythrityl hexacaprylate/hexacaprate • peg-100 stearate • trehalose • helianthus annuus (sunflower) seedcake • cetyl palmitate • sorbitol • sodium lactate • acetyl hexapeptide-8 • acrylates/c10-30 alkyl acrylate crosspolymer • sorbitan palmitate • sorbitan olivate • ethylhexylglycerin • sodium pca • pvp/hexadecene copolymer • sodium polyacrylate • propylene glycol dicaprate • sodium hyaluronate • isoceteth-20 • polyethylene • fragrance (parfum) • tetrahexyldecyl ascorbate • sodium hydroxide • sodium benzoate • disodium edta • bht • phenoxyethanol • chlorphenesin • yellow 5 (ci 19140) • red 4 (ci 14700) <iln44861>

Other information

protect the product in this container from excessive heat and direct sun

PRINCIPAL DISPLAY PANEL - 50 ml Jar Carton

ESTĒE LAUDER

Revitalizing Supreme +
Global Anti-Aging Cell Power Creme
Broad Spectrum SPF 15

All Skintypes

POIDS NET WT. 1.7 OZ./50 ml e